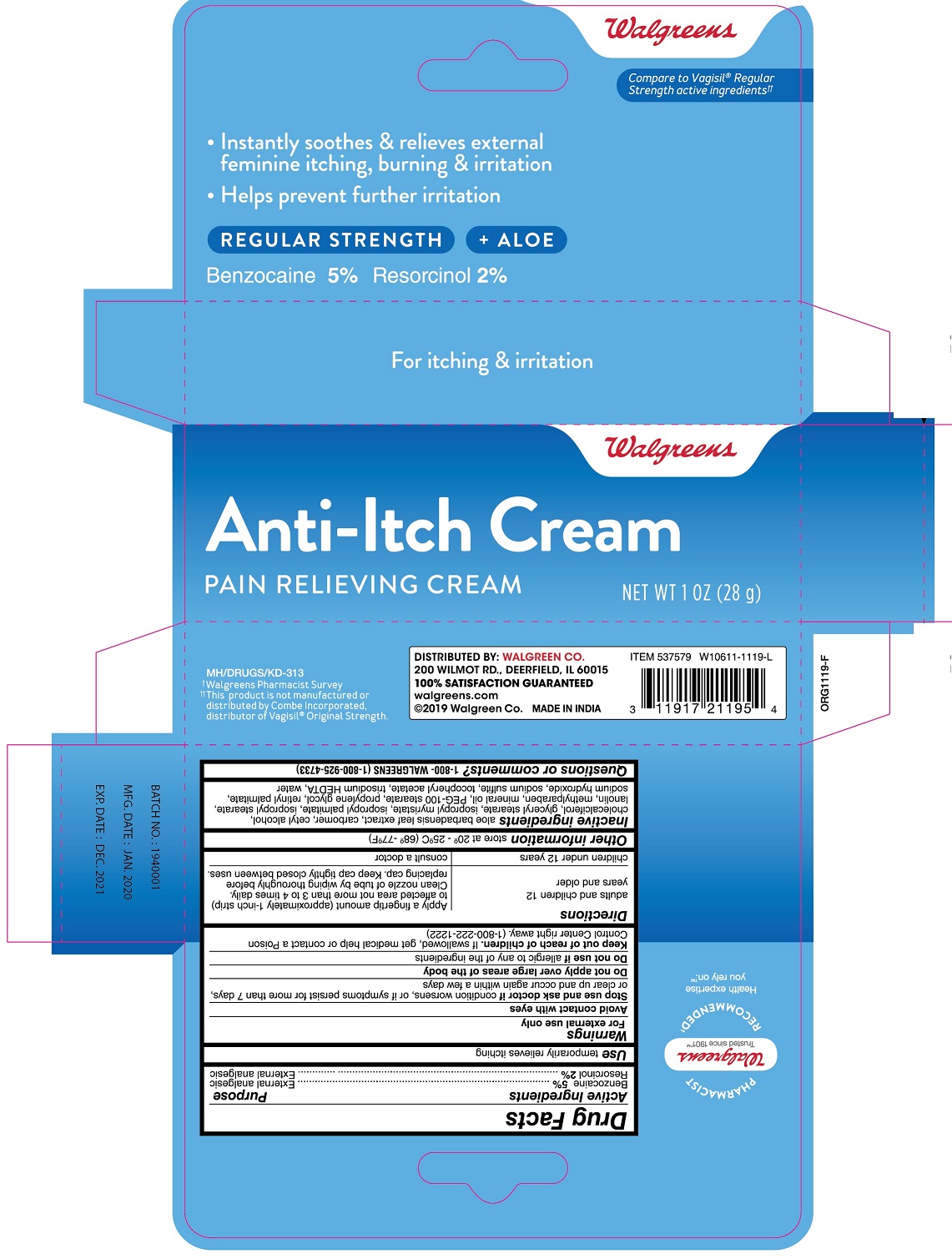 DRUG LABEL: Anti-Itch


NDC: 0363-0621 | Form: CREAM
Manufacturer: Walgreens
Category: otc | Type: HUMAN OTC DRUG LABEL
Date: 20220122

ACTIVE INGREDIENTS: BENZOCAINE 5 g/100 g; RESORCINOL 2 g/100 g
INACTIVE INGREDIENTS: ALOE VERA LEAF; CARBOMER HOMOPOLYMER, UNSPECIFIED TYPE; CETYL ALCOHOL; CHOLECALCIFEROL; GLYCERYL MONOSTEARATE; ISOPROPYL MYRISTATE; ISOPROPYL PALMITATE; ISOPROPYL STEARATE; LANOLIN; METHYLPARABEN; MINERAL OIL; PEG-100 STEARATE; PROPYLENE GLYCOL; VITAMIN A PALMITATE; SODIUM HYDROXIDE; SODIUM SULFITE; .ALPHA.-TOCOPHEROL ACETATE; TRISODIUM HEDTA; WATER

Anti-Itch Cream

Active ingredients

Benzocaine 5%

Resorcinol 2%

Purpose

External Analgesic

External Analgesic

Use

Temporarily relieves itching

Warnings

For external use only

WHEN USING

Avoid contact with eyes

Stop use and ask doctor if condition worsens, or if symptoms persist for more than 7 days or clear up and occur again within a few days.

Do not apply over large areas of the body.

Do not use if allergic to any of the ingredients

Keep out of reach of children. If swallowed, get medical help or contact a Poison Control Center right away. (1-800-222-1222)

Directions

adults and children 12 years and older

- apply a fingertip amount (approximately 1-inch strip) to affected area not more than 3 to 4 times daily.
- clean nozzle of tube by wiping thoroughly before replacing cap. Keep cap tightly closed between uses.

children under 12 years

- consult a doctor

Other information

store at 20°-25°C (68°-77°F)

Inactive ingredients

aloe barbadensis leaf extract, carbomer, cetyl alcohol, cholecalciferol, glyceryl stearate, isopropyl myristate, isopropyl palmitate, isopropyl stearate, lanolin, methylparaben, mineral oil, PEG-100 stearate, propylene glycol, retinyl palmitate, sodium hydroxide, sodium sulfite, tocopheryl acetate, trisodium HEDTA, water

Questions or comments

1-800-WALGREEN (1-800-925-4733)

Principal display panel - 28 g Carton Label

NDC 0363-0621-02

REGULAR STRENGTH

Anti-Itch Cream

Pain Relieving Cream

NET WT 1 OZ (28 g)